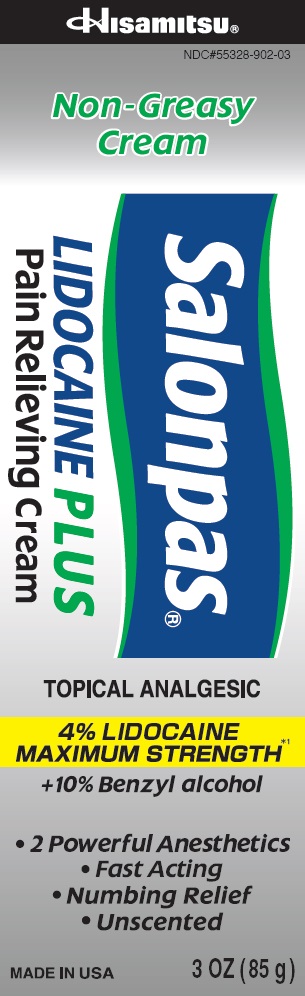 DRUG LABEL: Salonpas LIDOCAINE PLUS
NDC: 55328-902 | Form: CREAM
Manufacturer: Hisamitsu America, Inc.
Category: otc | Type: HUMAN OTC DRUG LABEL
Date: 20241203

ACTIVE INGREDIENTS: BENZYL ALCOHOL 10.0000 g/100 g; LIDOCAINE HYDROCHLORIDE 4.0000 g/100 g
INACTIVE INGREDIENTS: ALOE VERA LEAF; AMINOMETHYLPROPANOL; BUTYLENE GLYCOL; CETOSTEARYL ALCOHOL; DIHEXADECYL PHOSPHATE; alcohol; TERT-BUTYL ALCOHOL; DENATONIUM BENZOATE; SQUALANE; water

Active ingredients

Benzyl alcohol 10%

Lidocaine HCl 4%

Purpose

Topical anesthetic

Uses

For temporary relief of pain

Warnings

For external use only

Do not use

- on wounds or damaged skin
- in large quantities
- with a heating pad
- if you are allergic to any ingredients of this product

When using this product

- use only as directed
- avoid contact with the eyes, mucous membranes or rashes
- do not bandage tightly

Stop use and ask a doctor if

- skin reactions occur, such as rash, itching, redness, irritaion, pain, swelling and blistering
- conditions worsen
- symptoms persist for more than 7 days
- symptoms clear up and occur again within a few days

If pregnant or breast-feeding,

ask a health professional before use.

Keep out of reach of children.

If swallowed, get medical help or contact a Poison Control Center right away.

Directions

Adults and children 12 years of age and over:

- clean and dry affected area
- apply to affected area not more than 3 to 4 times daily

Children under 12 years of age:

consult a doctor

Other information

- Avoid storing product in direct sunlight
- Protect product from excessive moisture
- Store with lid closed tighly

Inactive ingredients

aloe barbadensis leaf juice, aminomethyl propanol, butylene glycol, carbomer copolymer, cetearyl alcohol, ceteth phosphate, dicetyl phosphate, dimethicone, glyceryl monostearate, hydroxyl acrylate/sodium acryloyldimethyl taurate copolymer, polysorbate, SD alcohol 40-B, squalane, steareth, water

Questions or comments?

Toll free 1-800-826-8861 www.salonpas.us

Principal Display Panel

Hisamitsu

NDC#55328-902-03

Non-Greasy Cream

Salonpas LIDOCAINE PLUS Pain Relieving Cream

TOPICAL ANALGESIC

4% LIDOCAIN MAXIMUM STRENGTH*1

plus 10% Benzyl alcohol

2 Powerful Anesthetics
Fast Acting
Numbing Relief
Unscented
MADE IN USA

3 OZ (85 g)